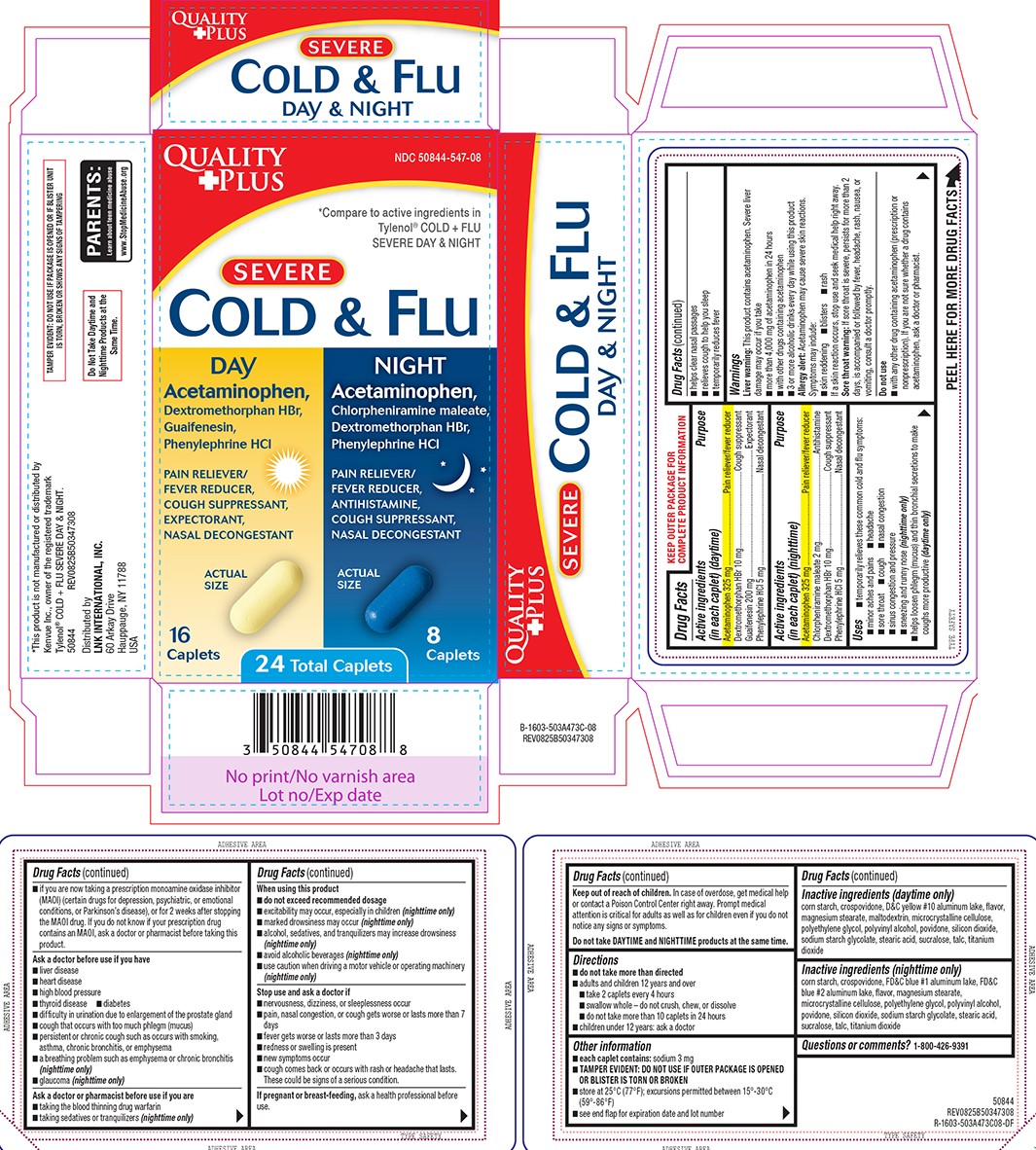 DRUG LABEL: Cold and Flu
NDC: 50844-547 | Form: KIT | Route: ORAL
Manufacturer: L.N.K. International, Inc.
Category: otc | Type: HUMAN OTC DRUG LABEL
Date: 20260217

ACTIVE INGREDIENTS: ACETAMINOPHEN 325 mg/1 1; DEXTROMETHORPHAN HYDROBROMIDE 10 mg/1 1; GUAIFENESIN 200 mg/1 1; PHENYLEPHRINE HYDROCHLORIDE 5 mg/1 1; ACETAMINOPHEN 325 mg/1 1; CHLORPHENIRAMINE MALEATE 2 mg/1 1; DEXTROMETHORPHAN HYDROBROMIDE 10 mg/1 1; PHENYLEPHRINE HYDROCHLORIDE 5 mg/1 1
INACTIVE INGREDIENTS: STARCH, CORN; CROSPOVIDONE, UNSPECIFIED; D&C YELLOW NO. 10 ALUMINUM LAKE; MAGNESIUM STEARATE; MALTODEXTRIN; MICROCRYSTALLINE CELLULOSE; POLYETHYLENE GLYCOL, UNSPECIFIED; POLYVINYL ALCOHOL, UNSPECIFIED; POVIDONE, UNSPECIFIED; SILICON DIOXIDE; SODIUM STARCH GLYCOLATE TYPE A POTATO; STEARIC ACID; SUCRALOSE; TALC; TITANIUM DIOXIDE; STARCH, CORN; CROSPOVIDONE, UNSPECIFIED; FD&C BLUE NO. 1 ALUMINUM LAKE; FD&C BLUE NO. 2 ALUMINUM LAKE; MAGNESIUM STEARATE; MICROCRYSTALLINE CELLULOSE; POLYETHYLENE GLYCOL, UNSPECIFIED; POLYVINYL ALCOHOL, UNSPECIFIED; POVIDONE, UNSPECIFIED; SILICON DIOXIDE; SODIUM STARCH GLYCOLATE TYPE A POTATO; STEARIC ACID; SUCRALOSE; TALC; TITANIUM DIOXIDE

Quality Plus 44-503A473C-08

Active ingredients (in each caplet) (daytime)

Acetaminophen 325 mg
Dextromethorphan HBr 10 mg
Guaifenesin 200 mg
Phenylephrine HCl 5 mg

Purpose

Pain reliever/fever reducer
Cough suppressant
Expectorant
Nasal decongestant

Active ingredients (in each caplet) (nighttime)

Acetaminophen 325 mg
Chlorpheniramine maleate 2 mg
Dextromethorphan HBr 10 mg
Phenylephrine HCl 5 mg

Purpose

Pain reliever/fever reducer
Antihistamine
Cough suppressant
Nasal decongestant

Uses

- temporarily relieves these common cold and flu symptoms:
  - cough
  - headache
  - sore throat
  - nasal congestion
  - minor aches and pains
  - sinus congestion and pressure
  - sneezing and runny nose (nighttime only)
- helps loosen phlegm (mucus) and thin bronchial secretions to make coughs more productive (daytime only)
- helps clear nasal passages
- relieves cough to help you sleep
- temporarily reduces fever

Warnings

Liver warning: This product contains acetaminophen. Severe liver damage may occur if you take

- more than 4,000 mg of acetaminophen in 24 hours
- with other drugs containing acetaminophen
- 3 or more alcoholic drinks every day while using this product

Allergy alert: Acetaminophen may cause severe skin reactions. Symptoms may include:

- skin reddening
- blisters
- rash

If a skin reaction occurs, stop use and seek medical help right away.

Sore throat warning: If sore throat is severe, persists for more than 2 days, is accompanied or followed by fever, headache, rash, nausea, or vomiting, consult a doctor promptly.

Do not use

- with any other drug containing acetaminophen (prescription or nonprescription). If you are not sure whether a drug contains acetaminophen, ask a doctor or pharmacist.
- if you are now taking a prescription monoamine oxidase inhibitor (MAOI) (certain drugs for depression, psychiatric, or emotional conditions, or Parkinson’s disease), or for 2 weeks after stopping the MAOI drug. If you do not know if your prescription drug contains an MAOI, ask a doctor or pharmacist before taking this product.

Ask a doctor before use if you have

- high blood pressure
- liver disease
- diabetes
- thyroid disease
- heart disease
- glaucoma (nighttime only)
- cough that occurs with too much phlegm (mucus)
- difficulty in urination due to enlargement of the prostate gland
- persistent or chronic cough such as occurs with smoking, asthma, chronic bronchitis, or emphysema
- a breathing problem such as emphysema or chronic bronchitis (nighttime only)

Ask a doctor or pharmacist before use if you are

- taking the blood thinning drug warfarin
- taking sedatives or tranquilizers (nighttime only)

When using this product

- do not exceed recommended dosage
- excitability may occur, especially in children (nighttime only)
- marked drowsiness may occur (nighttime only)
- avoid alcoholic beverages (nighttime only)
- use caution when driving a motor vehicle or operating machinery (nighttime only)
- alcohol, sedatives, and tranquilizers may increase drowsiness (nighttime only)

Stop use and ask a doctor if

- nervousness, dizziness, or sleeplessness occur
- pain, nasal congestion, or cough gets worse or lasts more than 7 days
- new symptoms occur
- fever gets worse or lasts more than 3 days
- redness or swelling is present
- cough comes back or occurs with rash or headache that lasts. These could be signs of a serious condition.

If pregnant or breast-feeding,

ask a health professional before use.

Keep out of reach of children.

In case of overdose, get medical help or contact a Poison Control Center right away. Prompt medical attention is critical for adults as well as for children even if you do not notice any signs or symptoms.

Do not take DAYTIME and NIGHTTIME products at the same time.

Directions

- do not take more than directed
- adults and children 12 years and over
  - take 2 caplets every 4 hours
  - swallow whole – do not crush, chew, or dissolve
  - do not take more than 10 caplets in 24 hours
- children under 12 years: ask a doctor

Other information

- each caplet contains: sodium 3 mg
- TAMPER EVIDENT: DO NOT USE IF OUTER PACKAGE IS OPENED OR BLISTER IS TORN OR BROKEN
- store at 25°C (77°F); excursions permitted between 15°-30°C (59°-86°F)
- see end flap for expiration date and lot number

Inactive ingredients (daytime only)

corn starch, crospovidone, D&C yellow #10 aluminum lake, flavor, magnesium stearate, maltodextrin, microcrystalline cellulose, polyethylene glycol, polyvinyl alcohol, povidone, silicon dioxide, sodium starch glycolate, stearic acid, sucralose, talc, titanium dioxide

Inactive ingredients (nighttime only)

corn starch, crospovidone, FD&C blue #1 aluminum lake, FD&C blue #2 aluminum lake, flavor, magnesium stearate, microcrystalline cellulose, polyethylene glycol, polyvinyl alcohol, povidone, silicon dioxide, sodium starch glycolate, stearic acid, sucralose, talc, titanium dioxide

Questions or comments?

1-800-426-9391

Principal display panel

QUALITY
+PLUS

NDC 50844-547-08

*Compare to active ingredients in
Tylenol® COLD + FLU
SEVERE DAY & NIGHT

SEVERE
COLD & FLU

DAY
Acetaminophen,
Dextromethorphan HBr,
Guaifenesin,
Phenylephrine HCl

PAIN RELIEVER/
FEVER REDUCER,
COUGH SUPPRESSANT,
EXPECTORANT,
NASAL DECONGESTANT

ACTUAL
SIZE

16
Caplets

NIGHT
Acetaminophen,
Chlorpheniramine maleate,
Dextromethorphan HBr,
Phenylephrine HCl

PAIN RELIEVER/
FEVER REDUCER,
ANTIHISTAMINE,
COUGH SUPPRESSANT,
NASAL DECONGESTANT

ACTUAL
SIZE

8
Caplets

24 Total Caplets

TAMPER EVIDENT: DO NOT USE IF PACKAGE IS OPENED OR IF BLISTER UNIT
IS TORN, BROKEN OR SHOWS ANY SIGNS OF TAMPERING

*This product is not manufactured or distributed by
Kenvue Inc., owner of the registered trademark
Tylenol® COLD + FLU SEVERE DAY & NIGHT.
50844 REV0825B50347308

Do Not Take Daytime and
Nighttime Products at the
Same Time.

Distributed by
LNK INTERNATIONAL, INC.
60 Arkay Drive
Hauppauge, NY 11788
USA

Quality plus 44-503A473C